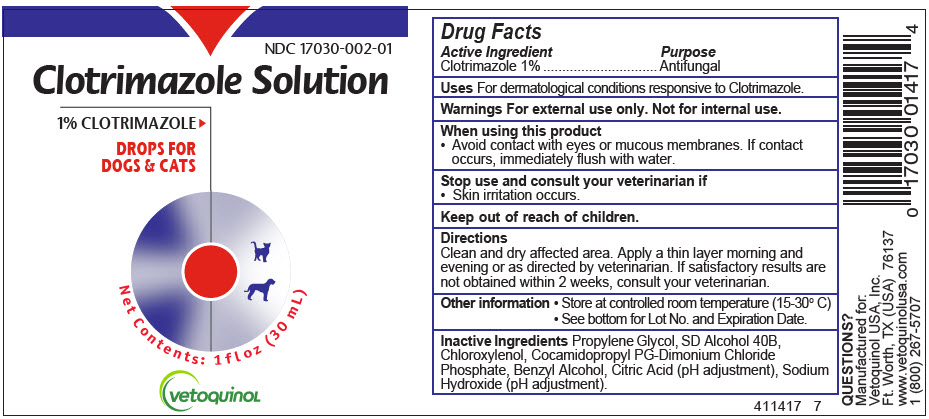 DRUG LABEL: Clotrimazole
NDC: 17030-002 | Form: SOLUTION/ DROPS
Manufacturer: Vetoquinol USA, Inc.
Category: animal | Type: OTC ANIMAL DRUG LABEL
Date: 20221209

ACTIVE INGREDIENTS: CLOTRIMAZOLE 10 mg/1 mL
INACTIVE INGREDIENTS: PROPYLENE GLYCOL; ALCOHOL; CHLOROXYLENOL; COCAMIDOPROPYL PROPYLENE GLYCOL-DIMONIUM CHLORIDE PHOSPHATE; PHOSPHATE ION; BENZYL ALCOHOL; CITRIC ACID MONOHYDRATE; SODIUM HYDROXIDE

Clotrimazole Solution (Drops)

Drug Facts

Active Ingredient

Clotrimazole, USP 1%

Purpose

Antifungal

Uses

For dermatological conditions responsive to Clotrimazole.

Warnings

For external use only. Not for internal use.

When using this product

- Avoid contact with eyes or mucous membranes. If contact occurs, immediately flush with water.

Stop use and consult your veterinarian if

- Skin irritation occurs.

Keep out of reach of children.

Directions

Clean and dry affected area. Apply a thin layer morning and evening or as directed by veterinarian. If satisfactory results are not obtained within 2 weeks, consult your veterinarian.

Other information

- Store at controlled room temperature (15-30° C)
- See bottom for Lot No. and Expiration Date.

Inactive Ingredients

Propylene Glycol, SD Alcohol 40B, Chloroxylenol, Cocamidopropyl PG-Dimonium Chloride Phosphate, Benzoyl Alcohol, Citric Acid (pH adjustment), Sodium Hydroxide (pH adjustment).

QUESTIONS?

Manufactured for:
Vetoquinol USA, Inc.
Ft. Worth, TX (USA) 76137
www.vetoquinolusa.com
1 (800) 267-5707

411417 7

PRINCIPAL DISPLAY PANEL - 30 mL Bottle Label

NDC 17030-002-01

Clotrimazole Solution

1% CLOTRIMAZOLE

DROPS FOR
DOGS & CATS

Net Contents: 1 fl oz (30 mL)

vetoquinoL